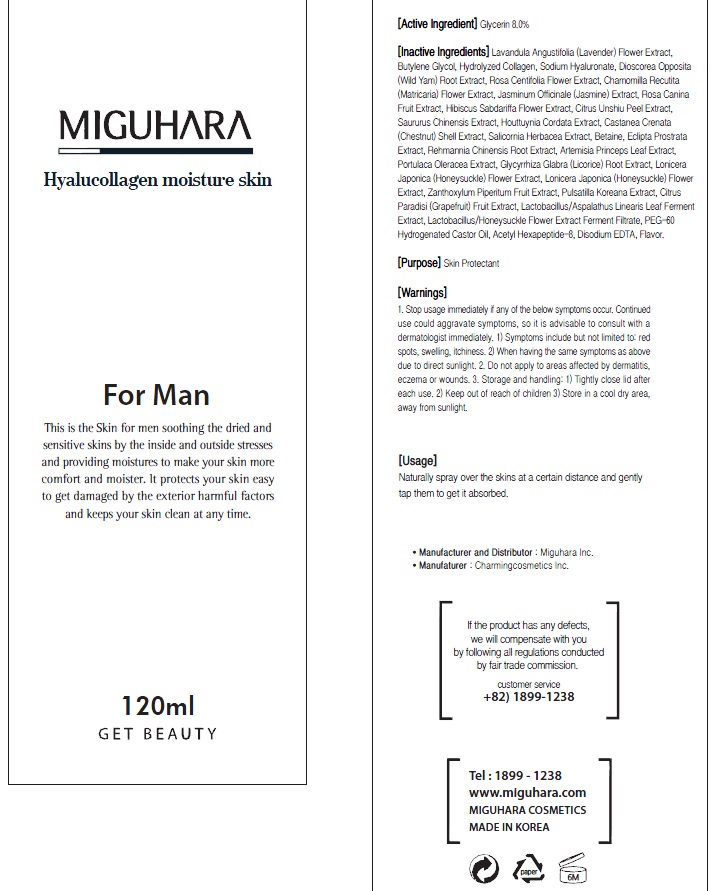 DRUG LABEL: Hyalucollagen Moisture Skin
NDC: 70380-220 | Form: SPRAY
Manufacturer: MIGUHARA
Category: otc | Type: HUMAN OTC DRUG LABEL
Date: 20160222

ACTIVE INGREDIENTS: Glycerin 12 g/150 mL
INACTIVE INGREDIENTS: LAVANDULA ANGUSTIFOLIA FLOWER; Butylene Glycol

ACTIVE INGREDIENT

Active Ingredient: Glycerin 8.0%

INACTIVE INGREDIENT

Inactive Ingredients: Lavandula Angustifolia (Lavender) Flower Extract, Butylene Glycol, Hydrolyzed Collagen, Sodium Hyaluronate, Dioscorea Opposita (Wild Yam) Root Extract, Rosa Centifolia Flower Extract, Chamomilla Recutita (Matricaria) Flower Extract, Jasminum Officinale (Jasmine) Extract, Rosa Canina Fruit Extract, Hibiscus Sabdariffa Flower Extract, Citrus Unshiu Peel Extract, Saururus Chinensis Extract, Houttuynia Cordata Extract, Castanea Crenata (Chestnut) Shell Extract, Salicornia Herbacea Extract, Betaine, Eclipta Prostrata Extract, Rehmannia Chinensis Root Extract, Artemisia Princeps Leaf Extract, Portulaca Oleracea Extract, Glycyrrhiza Glabra (Licorice) Root Extract, Lonicera Japonica (Honeysuckle) Flower Extract, Lonicera Japonica (Honeysuckle) Flower Extract, Zanthoxylum Piperitum Fruit Extract, Pulsatilla Koreana Extract, Citrus Paradisi (Grapefruit) Fruit Extract, Lactobacillus/Aspalathus Linearis Leaf Ferment Extract, Lactobacillus/Honeysuckle Flower Extract Ferment Filtrate, PEG-60 Hydrogenated Castor Oil, Acetyl Hexapeptide-8, Disodium EDTA, Flavor

PURPOSE

Purpose: Skin Protectant

WARNINGS

1. Stop usage immediately if any of the below symptoms occur. Continued use could aggravate symptoms, so it is advisable to consult with a dermatologist immediately. 1) Symptoms include but not limited to: red spots, swelling, itchiness. 2) When having the same symptoms as above due to direct sunlight. 2. Do not apply to areas affected by dermatitis, eczema or wounds. 3. Storage and handling: 1) Tightly close lid after each use. 2 Keep out of reach of children 3) Store in a cool dry area, away from sunlight

KEEP OUT OF REACH OF CHILDREN

Usage

Usage: Naturally spray over the skins at a certain distance and gently tap them to get it absorbed.

Usage

Usage: Naturally spray over the skins at a certain distance and gently tap them to get it absorbed.